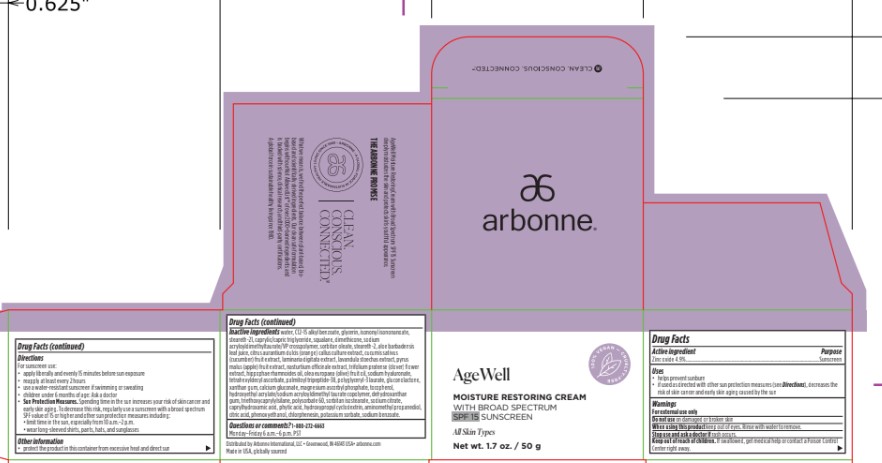 DRUG LABEL: Arbonne AgeWell Moisture Restoring Broad Spectrum SPF 15 Sunscreen
NDC: 42508-820 | Form: CREAM
Manufacturer: Arbonne International, LLC
Category: otc | Type: HUMAN OTC DRUG LABEL
Date: 20241112

ACTIVE INGREDIENTS: ZINC OXIDE 49 mg/1 g
INACTIVE INGREDIENTS: WATER; ALKYL (C12-15) BENZOATE; GLYCERIN; ISONONYL ISONONANOATE; STEARETH-21; MEDIUM-CHAIN TRIGLYCERIDES; SQUALANE; DIMETHICONE; SORBITAN MONOOLEATE; STEARETH-2; ALOE VERA LEAF; CUCUMBER; LAMINARIA DIGITATA; LAVANDULA STOECHAS FLOWERING TOP; APPLE; NASTURTIUM OFFICINALE; TRIFOLIUM PRATENSE FLOWER; HIPPOPHAE RHAMNOIDES SEED OIL; OLIVE OIL; HYALURONATE SODIUM; TETRAHEXYLDECYL ASCORBATE; PALMITOYL LYSYLDIOXYMETHIONYLLYSINE; POLYGLYCERYL-3 LAURATE; GLUCONOLACTONE; XANTHAN GUM; CALCIUM GLUCONATE; MAGNESIUM ASCORBYL PHOSPHATE; TOCOPHEROL; HYDROXYETHYL ACRYLATE/SODIUM ACRYLOYLDIMETHYL TAURATE COPOLYMER (100000 MPA.S AT 1.5%); DEHYDROXANTHAN GUM; TRIETHOXYCAPRYLYLSILANE; POLYSORBATE 60; SORBITAN ISOSTEARATE; TRISODIUM CITRATE DIHYDRATE; CAPRYLHYDROXAMIC ACID; FYTIC ACID; HYDROXYPROPYL BETADEX; AMINOMETHYL PROPANEDIOL; ANHYDROUS CITRIC ACID; PHENOXYETHANOL; CHLORPHENESIN; POTASSIUM SORBATE; SODIUM BENZOATE

Arbonne®AgeWell Moisture Restoring Broad Spectrum SPF 15 Sunscreen

Drug Facts

Active ingredient

Zinc oxide 4.9%

Purpose

Sunscreen

Uses

- helps prevent sunburn
- if used as directed with other sun protection measures (see Directions), decreases the risk of skin cancer and early skin aging caused by the sun

Warnings

For external use only

Do not useon damaged or broken skin

WHEN USING

When using this productkeep out of eyes. Rinse with water to remove.

Stop use and ask a doctor ifrash occurs.

Keep out of reach of children.If swallowed, get medical help or contact a Poison Control Center right away.

Directions

For sunscreen use:

- apply liberally and evenly 15 minutes before sun exposure
- reapply at least every 2 hours
- use a water-resistant sunscreen if swimming or sweating
- children under 6 months of age: Ask a doctor
- Sun Protection Measures.Spending time in the sun increases your risk of skin cancer and early skin aging. To decrease this risk, regularly use a sunscreen with a broad spectrum SPF value of 15 or higher and other sun protection measures including:
  - limit time in the sun, especially from 10 a.m.–2 p.m.
  - wear long-sleeved shirts, pants, hats, and sunglasses

Other information

- protect the product in this container from excessive heat and direct sun

Inactive ingredients

water, C12-15 alkyl benzoate, glycerin, isononyl isononanoate, steareth-21, caprylic/capric triglyceride, squalane, dimethicone, sodium acryloyldimethyltaurate/VP crosspolymer, sorbitan oleate, steareth-2, aloe barbadensis leaf juice, citrus aurantium dulcis (orange) callus culture extract, cucumis sativus (cucumber) fruit extract, laminaria digitata extract, lavandula stoechas extract, pyrus malus (apple) fruit extract, nasturtium officinale extract, trifolium pratense (clover) flower extract, hippophae rhamnoides oil, olea europaea (olive) fruit oil, sodium hyaluronate, tetrahexyldecyl ascorbate, palmitoyl tripeptide-38, polyglyceryl-3 laurate, gluconolactone, xanthan gum, calcium gluconate, magnesium ascorbyl phosphate, tocopherol, hydroxyethyl acrylate/sodium acryloyldimethyl taurate copolymer, dehydroxanthan gum, triethoxycaprylylsilane, polysorbate 60, sorbitan isostearate, sodium citrate, caprylhydroxamic acid, phytic acid, hydroxypropyl cyclodextrin, aminomethyl propanediol, citric acid, phenoxyethanol, chlorphenesin, potassium sorbate, sodium benzoate.

Questions or comments?

1-800-272-6663Monday–Friday 6 a.m.–6 p.m. PST

Distributed by Arbonne International, LLC • Greenwood, IN 46143 USA

PRINCIPAL DISPLAY PANEL - 50 g Jar Carton

AgeWell

100% VEGAN – CRUELTY-FREE

MOISTURE RESTORING CREAM
WITH BROAD SPECTRUM
SPF 15 SUNSCREEN

All Skin Types

Net wt. 1.7 oz. / 50 g